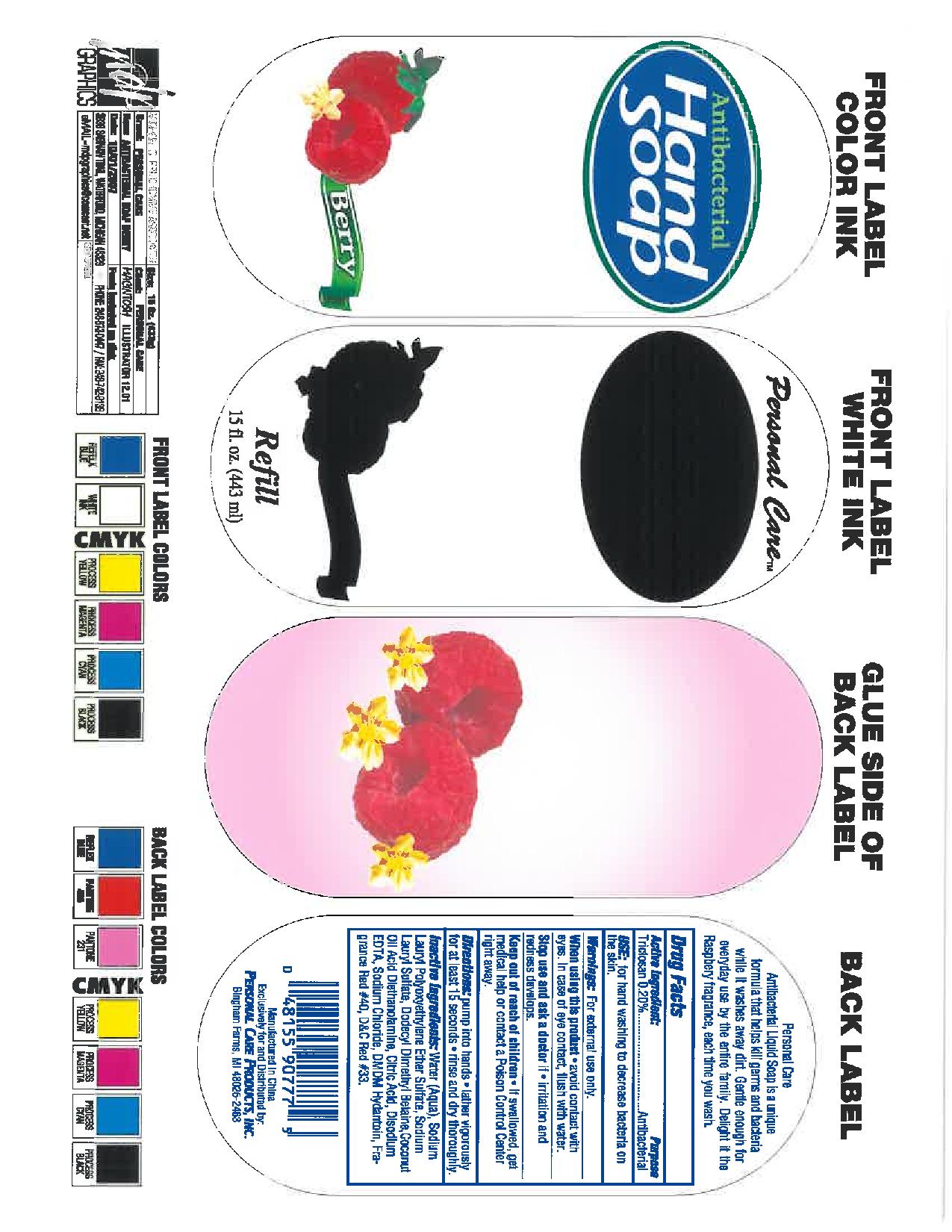 DRUG LABEL: antibacterial hand
NDC: 29500-9077 | Form: SOAP
Manufacturer: Personal Care Products
Category: otc | Type: HUMAN OTC DRUG LABEL
Date: 20111026

ACTIVE INGREDIENTS: TRICLOSAN .886 mL/443 mL
INACTIVE INGREDIENTS: WATER; ETHER; SODIUM LAURYL SULFATE; BETAINE; DIETHANOLAMINE; CITRIC ACID MONOHYDRATE; EDETATE DISODIUM; SODIUM CHLORIDE; DMDM HYDANTOIN; D&C RED NO. 33

antibacterial hand

Active ingredient:

Triclosan .2%

Purpose: Antibacterial

Keep out of reach of children. If swallowed, get medical help or contact a Poison Control Center right away.

INDICATIONS AND USAGE

Use: for hand washing to decrease bacteria on the skin.

Warnings:

For external use only.

When using this product avoid contact with eyes. In case of eye contact, flush with water.

Stop use and ask a doctor if irritation and redness develops.

DOSAGE AND ADMINISTRATION

Directions: pump into hands, lather vigorously for at least 15 seconds, rinse and dry thoroughly.

INACTIVE INGREDIENT

Inactive ingredients: water (aqua), sodium lauryl polyoxyethylene ether sulfate, sodium lauryl sulfate, dodecyl dimethyl betaine, coconut oil acid diethanolamine, citric acid, disodium edta, sodium chloride, DMDM hydantoin, fragrance, red 40, D and C red 33

PACKAGE LABEL

Personal Care antibacterial hand soap

berry

refill

15 fl. oz (443 ml)